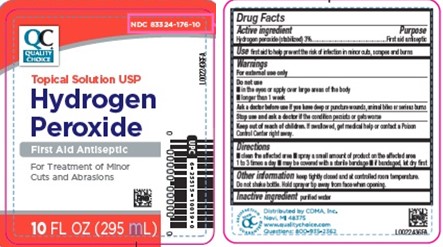 DRUG LABEL: Hydrogen Peroxide
NDC: 83324-176 | Form: SOLUTION
Manufacturer: Chain Drug Marketing Association
Category: otc | Type: HUMAN OTC DRUG LABEL
Date: 20260227

ACTIVE INGREDIENTS: HYDROGEN PEROXIDE 30 mg/1 mL
INACTIVE INGREDIENTS: WATER

Quality Choice 871.001/871AA
Hydrogen Peroxide

Active ingredient

Hydrogen peroxide (stabilized) 3%

Purpose

First aid antiseptic

Uses

- first aid to help prevent the rise of infection in minor cuts, scrapes and burns

Warnings

For external use only

Do not use

• in the eyes or apply over large areas of the body
• longer than 1 week

Ask a doctor before use if

you have deep or puncture wounds, animal bites or serious burns

Stop use and ask a doctor if

• the condition persists or gets worse

Keep out of reach of children.

If swallowed, get medical help or contact a Poison Control Center right away.

Directions

- clean the affected area
- apply a small amount of product on the affected area 1 to 3 times a day
- may be covered with a sterile bandage
- if bandaged, let dry first

Other information

keep tightly closed and at controlled room temperature. Do not shake bottle. Hold away from face when opening.

Inactive ingredient

purified water

Adverse reaction

Distributed by CDMA

Novi, MI 48375

www.qualitychoice.com

Questions: 800-935-2362

principal display panel

NDC 83324-176-10

QC®

QUALITY CHOICE

Topical Solution USP

Hydrogen Peroxide

First Aid Antiseptic

For Treatment of Minor Cuts and Abrasions

10 FL OZ (236 mL)